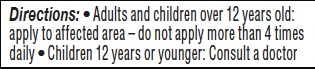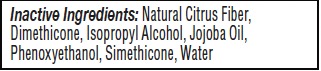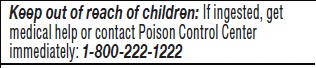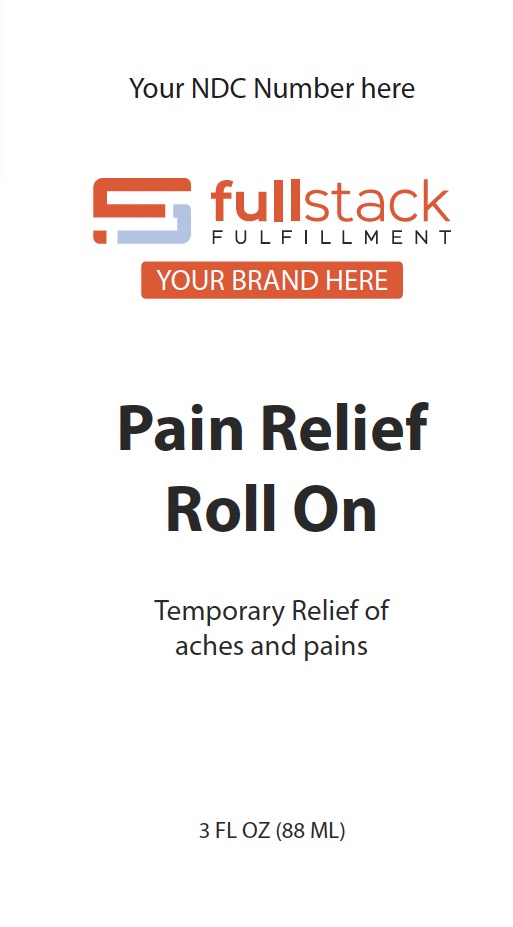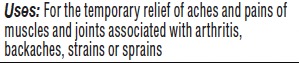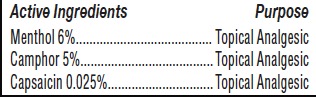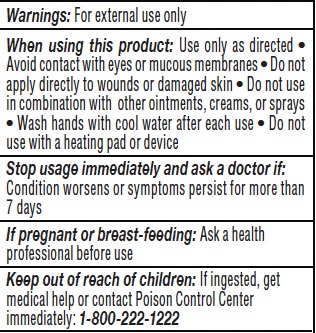 DRUG LABEL: Pain Relief Roll On
NDC: 84890-282 | Form: LIQUID
Manufacturer: Fit Life Health, LLC
Category: otc | Type: HUMAN OTC DRUG LABEL
Date: 20241107

ACTIVE INGREDIENTS: CAMPHOR (SYNTHETIC) 0.05 g/1 g; MENTHOL 0.06 g/1 g; CAPSAICIN 0.00025 g/1 g
INACTIVE INGREDIENTS: ISOPROPYL ALCOHOL; DIMETHICONE; PHENOXYETHANOL; SILICON DIOXIDE; CITRUS FRUIT; JOJOBA OIL; WATER

Inactive ingredients Section

Inactive Ingredients: Natural Citrus Fiber,

Dimethicone, Isopropyl Alcohol, Jojoba Oil,

Phenoxyethanol, Simethicone, Water

Active Ingredient Section see CapsaicinLabel.jpg

Menthol 6%........................................ Topical Analgesic

Camphor 5%....................................... Topical Analgesic

Capsaicin 0.025%............................... Topical Analgesic

Dosage And Administration

Directions: • Adults and children over 12 years old:

apply to affected area – do not apply more than 4 times

daily • Children 12 years or younger: Consult a doctor

Warnings

Warning And Precautions

INDICATIONS AND USAGE

Uses: For the temporary relief of aches and pains of

muscles and joints associated with arthritis,

backaches, strains or sprains

Keep Out Of Reach Of Children

Keep out of reach of children: If ingested, get
medical help or contact Poison Control Center
immediately: 1-800-222-1222

Purpose Section

For the temporary relief of aches and pains of

muscles and joints associated with arthritis,

backaches, strains or sprains

Primary Label

Temporary Relief of

aches and pains

3 FL OZ (88 ML)